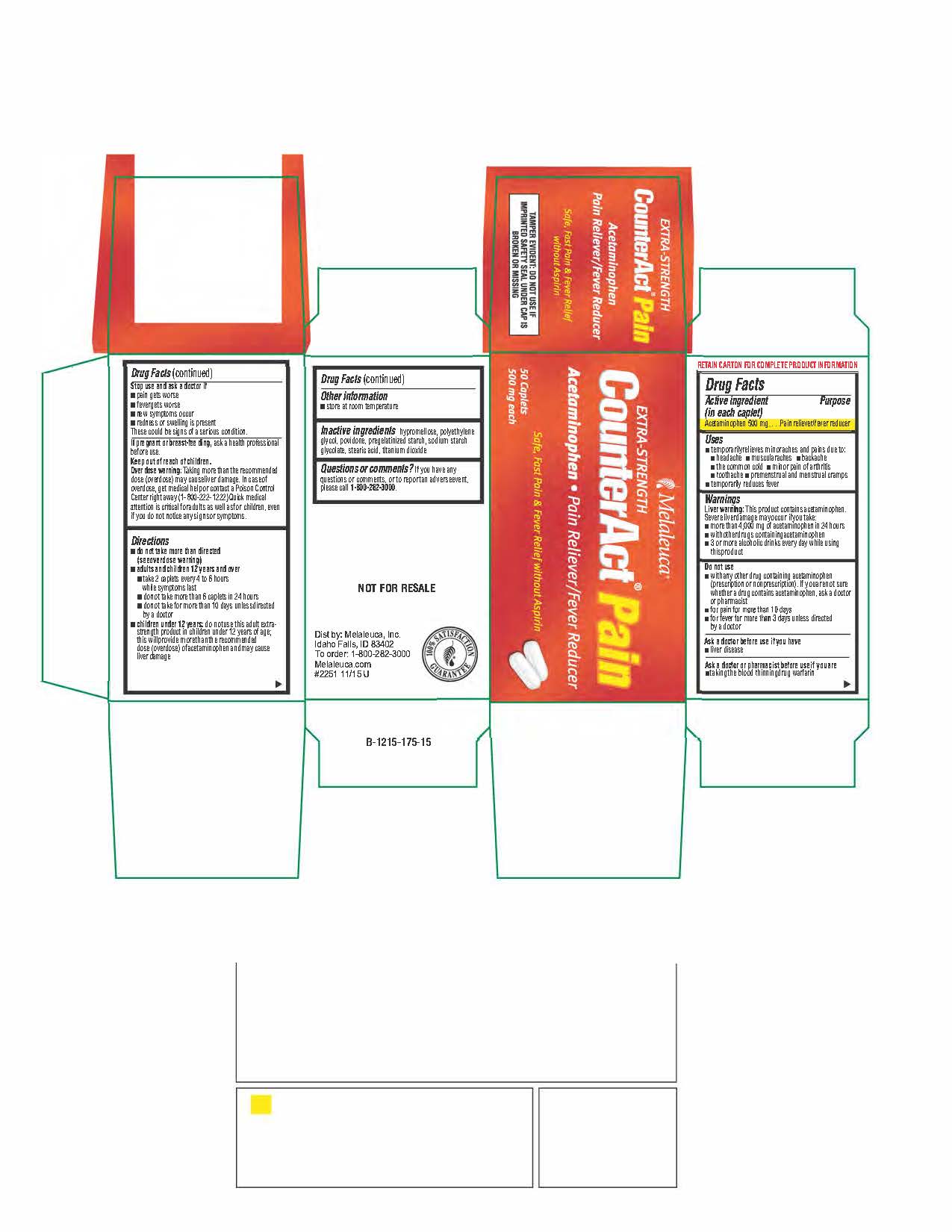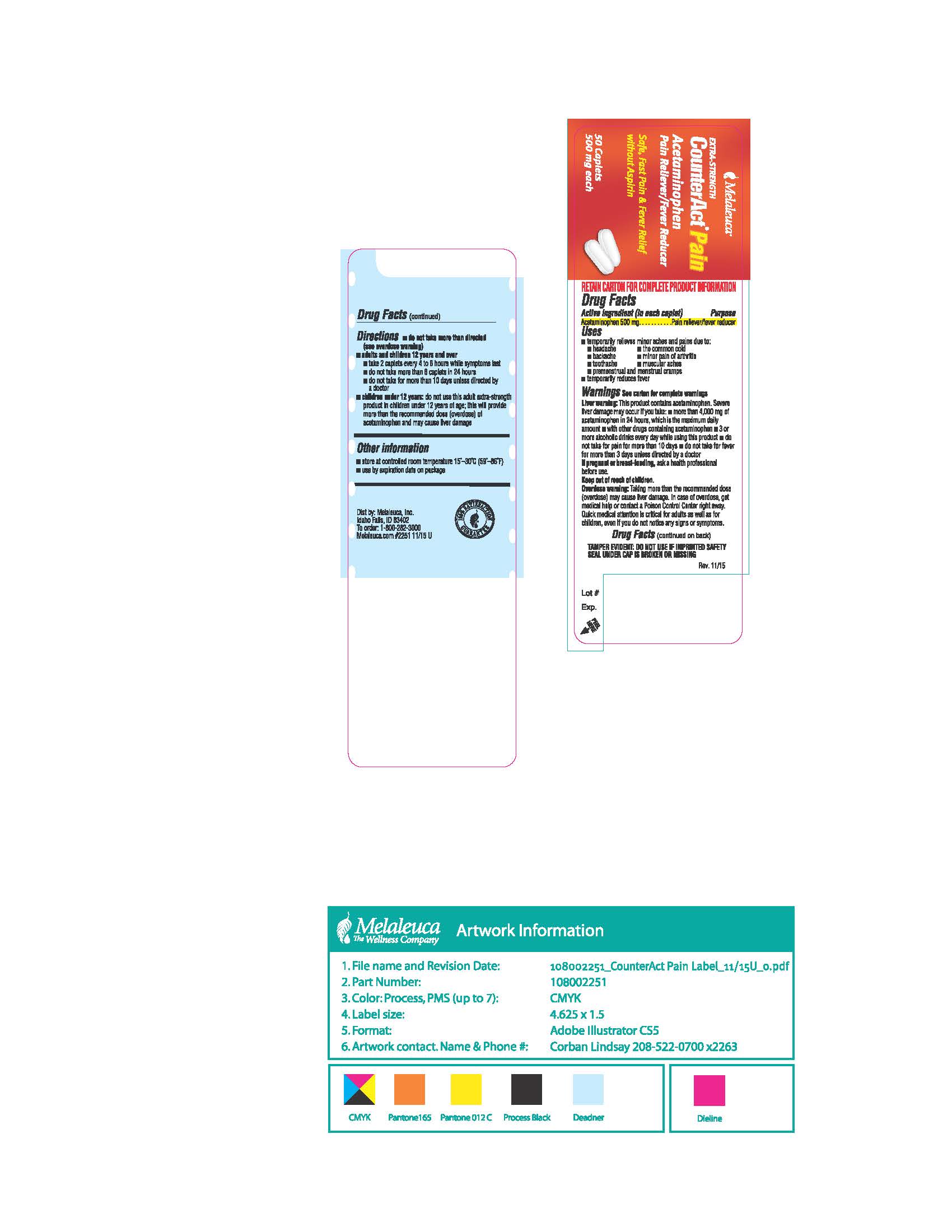 DRUG LABEL: CounterAct
NDC: 54473-305 | Form: TABLET, FILM COATED
Manufacturer: Melaleuca, Inc.
Category: otc | Type: HUMAN OTC DRUG LABEL
Date: 20250320

ACTIVE INGREDIENTS: ACETAMINOPHEN 500 mg/1 1
INACTIVE INGREDIENTS: TITANIUM DIOXIDE; HYPROMELLOSES; POLYETHYLENE GLYCOL; POVIDONE; STARCH, CORN; SODIUM STARCH GLYCOLATE TYPE A POTATO; STEARIC ACID

CounterAct Pain Content of Labeling

Active Ingredients (in each caplet)
Acetaminophen 500 mg

Purposes
Pain Reliever/fever reducer

Uses

- for the temporary relief of minor aches and pains due to:
-
  - headache
  - the common cold
  - backache
  - minor pain of arthritis
  - toothache
  - muscular aches
  - premenstrual and menstrual cramps
- temporarily reduces fever

Warnings
Liver Warning: This product contains acetaminophen. Severe liver damage may occur if you take:

- more than 8 caplets in 24 hours, which is the maximum daily amount
- with other drugs containing acetaminophen
- 3 or more alcoholic drinks every day while using this product

Do not use

- with any other drug containing acetaminophen (prescription or nonprescription). If you are not sure whether a drug contains acetaminophen, ask a doctor or pharmacist.

Ask a doctor before use if you have

- liver disease

Ask a doctor or pharmacist before use if you are

- taking the blood thinning drug warfarin

Stop use and ask a doctor if:

- pain gets worse or lasts more than 10 days
- fever gets worse or lasts more than 3 days
- new symptoms occur redness or swelling is present

These could be signs of a serious condition

PREGNANCY OR BREAST FEEDING

If pregnant or breast-feeding, ask a health professional before use.

Keep out of reach of children.

OVERDOSAGE

Overdose warning: Taking more than the recommended dose (overdose) may cause liver damage. In case of overdose, get medical help or contact a Poison Control Center right away. (1-800-222-1222). Quick medical attention is critical for adults as well as for children even if you do not notice any signs or symptoms.

Directions

- do not take more than directed (see overdose warning)
- adults and children 12 years and over
-
  - take 2 caplets every 4 to 6 hours while symptoms last
  - do not take more than 8 caplets in 24 hours
  - do not take more than 10 days unless directed by a doctor
- children under 12 years: do not use this adult extra strength product in children under 12 years of age; this will provide more than the recommended dose (overdose) of acetaminophen and may cause liver damage

Other information

- store at room temperature

INACTIVE INGREDIENT

Inactive ingredients Hypromellose, Polyethylene Glycol, Povidone, Pregelatinized Starch, Sodium Starch Glycolate, Stearic Acid.

Questions or comments? If you have any questions or comments, or to report and adverse event, please contact 1-800-282-3000.

BOXED WARNING

TAMPER EVIDENT: DO NOT USE IF IMPRINTED SAFETY SEAL UNDER CAP IS BROKEN OR MISSING